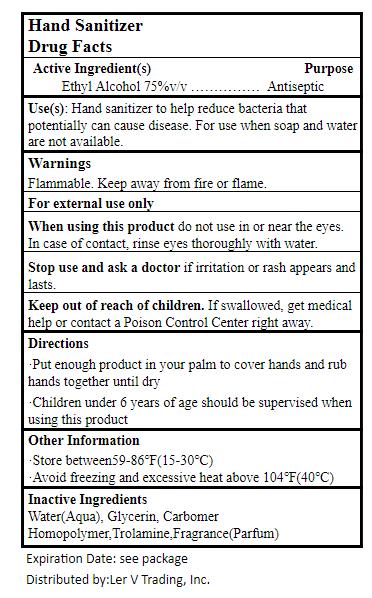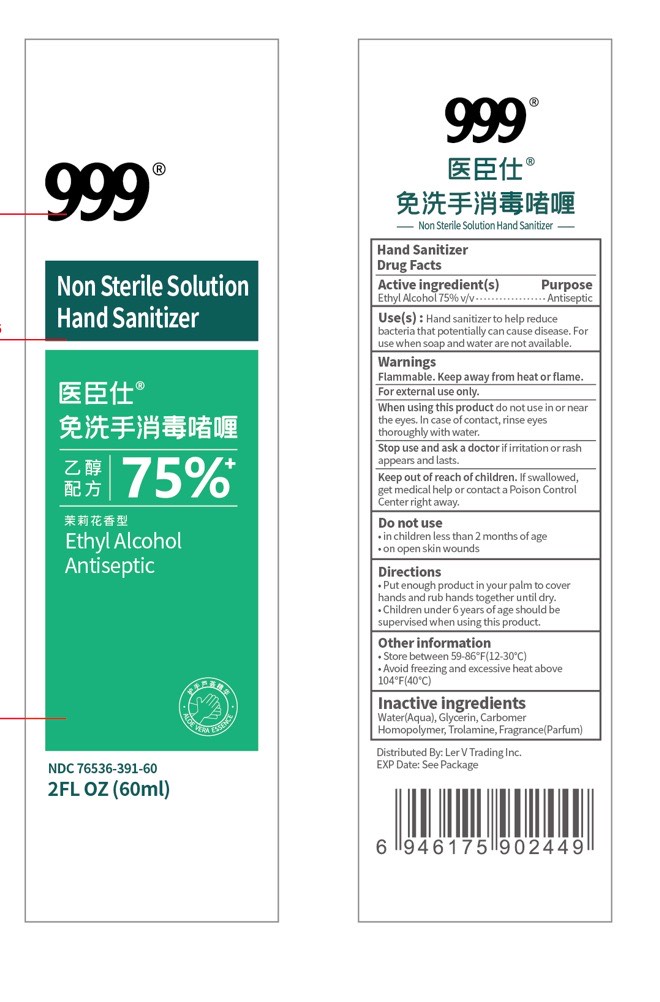 DRUG LABEL: 999 Hand Sanitizer
NDC: 76536-391 | Form: LIQUID
Manufacturer: LER V TRADING INC.
Category: otc | Type: HUMAN OTC DRUG LABEL
Date: 20200428

ACTIVE INGREDIENTS: ALCOHOL 75 mL/100 mL
INACTIVE INGREDIENTS: GLYCERIN; CARBOMER HOMOPOLYMER, UNSPECIFIED TYPE; TROLAMINE; WATER

Active Ingredient

Ethyl Alcohol 75 % v/v.

Purpose

Antiseptic

Uses

Hand sanitizer to help reduce bacteria on the skin.

Warnings

Flammable. Keep away from fire or flame.

For external use only.

When using this product, do not use in or near the eyes. In case of contact, rinse eyes thoroughly with water.
Stop use and ask a doctor if irritation or rash appears and lasts.

Keep out of reach of children. If swallowed, get medical help or contact a Poison Control Center right away.

Directions

- Put enough product in your palm to cover hands and rub hands together briskly until dry.

Inactive ingredients

Water(Aqua), Glycerin, Carbomer Homopolymer, Trolamine, Fragrance (Parfum).

Other Information

STORE BETWEEN 59-86℉(15-30℃)

AVOID FREEZING AND EXCESSIVE HEAT ABOVE 140℉(40℃)

EXP DATE: SEE ON PACKAGE